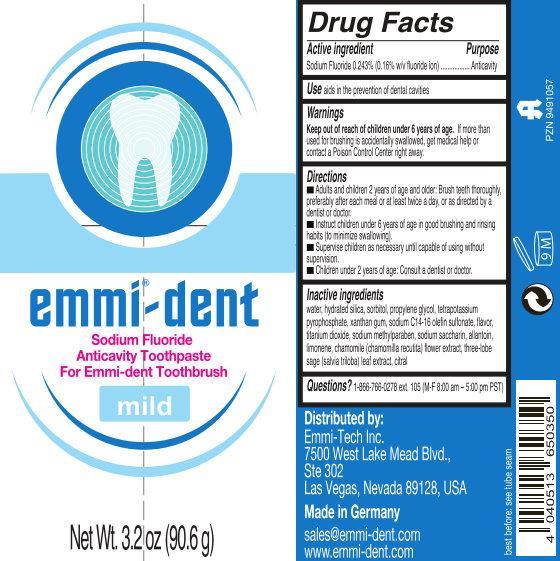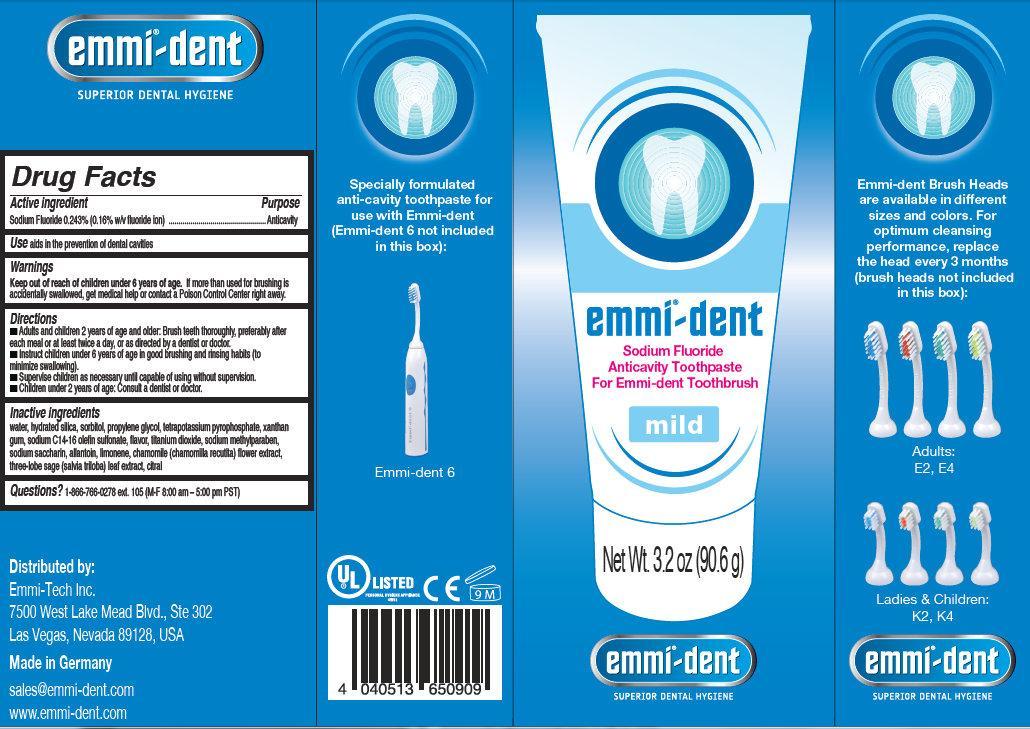 DRUG LABEL: emmi dent Sodium Fluoride Anticavity Mild
NDC: 63956-001 | Form: PASTE, DENTIFRICE
Manufacturer: EMAG AG
Category: otc | Type: HUMAN OTC DRUG LABEL
Date: 20140422

ACTIVE INGREDIENTS: SODIUM FLUORIDE 0.16 g/100 g
INACTIVE INGREDIENTS: WATER; HYDRATED SILICA; SORBITOL; PROPYLENE GLYCOL; POTASSIUM PYROPHOSPHATE; XANTHAN GUM; SODIUM C14-16 OLEFIN SULFONATE; TITANIUM DIOXIDE; METHYLPARABEN SODIUM; SACCHARIN SODIUM; ALLANTOIN; LIMONEN-10-OL, (+)-; CHAMOMILE; THREE-LOBE SAGE; CITRAL

emmi dent Sodium Fluoride Anticavity Toothpaste

Active Ingredient

Sodium fluoride 0.243% (0.16 w/v fluoride ion)

Purpose

Anticavity

Use

Aids in the prevention of dental cavities.

Warnings

Keep out of reach of children under 6 years of age. If more than used for brushing is accidentally swallowed, get medical help or contact a Poison Control Center right away.

Directions

- Adults and children 2 years and older: Brush teeth thoroughly, preferably after each meal or at least twice a day, or as directed by a dentist or doctor.
- Instruct children under 6 years of age in good brushing and rinsing habits (to minimize swallowing).
- Supervise children as necessary until capable of using without supervision.
- Children under 2 years: Consult a dentist or doctor.

Inactive Ingredients

water, hydrated silica, sorbitol, propylene glycol, tetrapotassium pyrophosphate, xanthan, gum, sodium C14-16 olefin sulfonate, flavor, titanium dioxide, sodium methylparaben, sodium saccharin, allantoin, limonene, chamomile (chamomilla recutita) flower extract, three-lobe sage (salvia triloba) leaf extract, citral